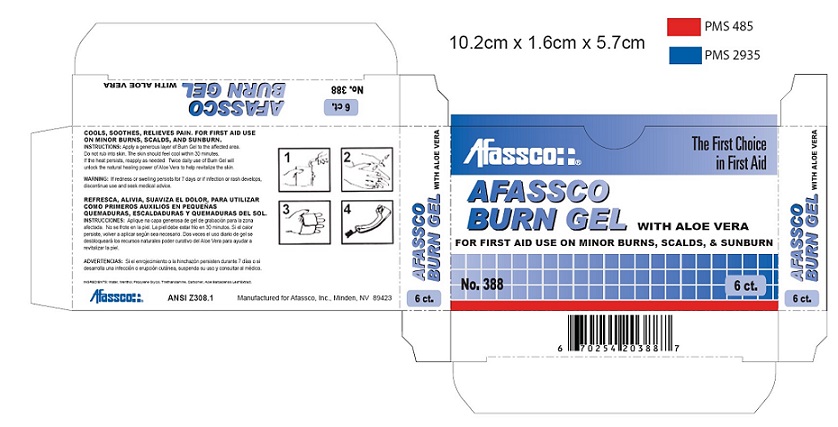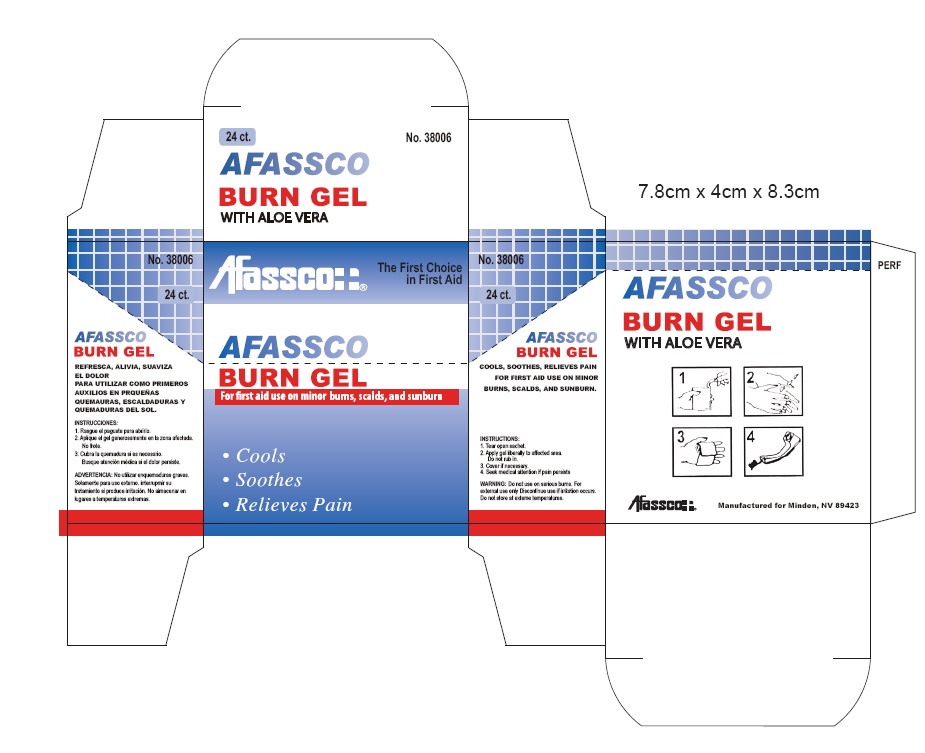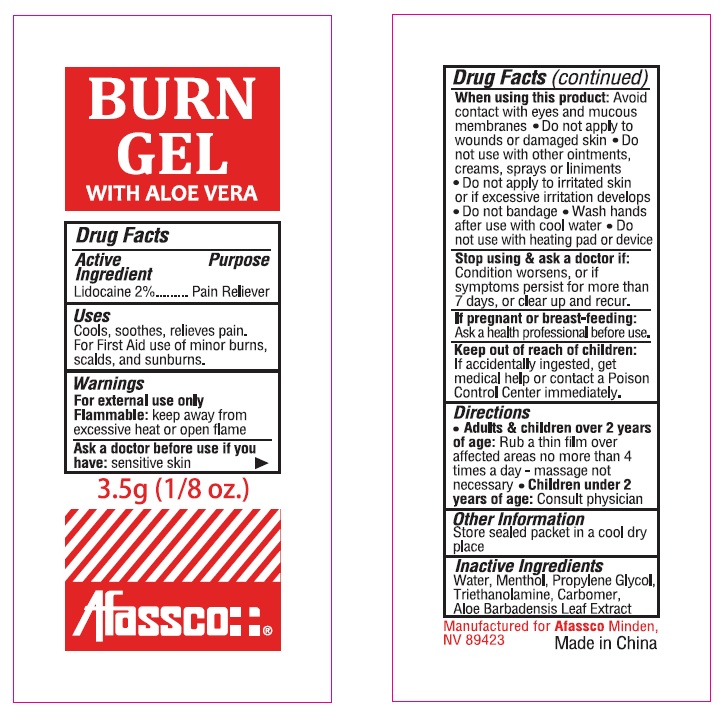 DRUG LABEL: Afassco Burn Gel
NDC: 51532-3806 | Form: GEL
Manufacturer: Afassco Inc.
Category: otc | Type: HUMAN OTC DRUG LABEL
Date: 20230112

ACTIVE INGREDIENTS: LIDOCAINE 70 mg/3.5 g
INACTIVE INGREDIENTS: WATER; MENTHOL; PROPYLENE GLYCOL; TROLAMINE; CARBOMER 1342; ALOE VERA LEAF

Afassco Burn Gel

Drug Facts

Active ingredient

lidocaine 2%

Purpose

Pain Reliever

Uses

Cools, soothes, relieves pain,

For First Aid Use of minor burns,

scalds, and sunburns.

Warnings

For external use only.

Flammable: Keep away from

excessine heat or open flame

Ask a doctor before use if you

have: sensitive skin

When using this product: Avoid

contact with eyes and mucos

membranes ● Do not apply to

wounds or damaged skin ● Do

not apply to irritated skin

or if excessive irritation develops

● Do not bandage ● Wash hands

after use with cool water ● Do

not use with heating pad or device

Slop use and & a doctor if:

Condition worsens, or if

symptoms persist for more than

7 days, or clear up and recur.

If pregnant or breast feeding:

Ask a health professional before use.

Keep out of reach of children:

If accidentally ingested, get

medical help or contact a Poison

Control Center immediately.

Directions

● Adults & children over 2 years

of age: Rub a thin film over

affected areas no more than 4

times a day - massage not

necessary ● Children under 2

years of age: Consult a physician

Other information

Store sealed packet in a cool dry place

Inactive ingredients

Water, Menthol, Propylene Glycol,

Triethanolamine, Carbomer,

Aloe Barbadensis Leaf Extract

Package Labeling

Afassco¦ ¦®

The First Choice

in First Aid

AFASSCO

BURN GEL WITH ALOE VERA

FOR FIRST AID USE ON MINOR BURNS, SCALDS, & SUNBURN

No.388 6 ct.

AFASSCO

BURN GELWITH ALOE VERA

6 ct.

AFASSCO

BURN GELWITH ALOE VERA

6 ct.

COOLS, SOOTHES, RELIEVES PAIN. FOR FIRST AID USE
ON MINOR BURNS, SCALDS, AND SUNBURN.

INSTRUCTIONS: Apply a generous layer of Burn Gel to the affected area.
Do not rub into skin. The skin should feel cool within 30 minutes.
If the heat persists, reapply as needed. Twice daily use of Burn Gel will
unlock the natural healing power of Aloe Vera to help revitalize the skin.

WARNING: If redness or swelling persists for 7 days or if infection or rash develops,
discontinue use and seek medical advice.

REFRESCA, ALIVIA, SUAVIZA EL DOLOR, PARA UTILIZAR
COMO PRIMEROS AUXILIOS EN PEQUEÑAS
QUEMADURAS, ESCALDADURAS Y QUEMADURAS DEL SOL.

INSTRUCCIONES: Aplique na capa generosa de gel de grabación para la zona
afectada. No se frote en la piel. La piel debe estar frio en 30 minutos. Si el calor
persiste, volver a aplicar según sea necesario. Dos veces el uso diario de gel se
desbloqueará los recursos naturales poder curativo del Aloe Vera para ayudar a
revitalizar la piel.

ADVERTENCIAS: Si el enrojecimiento o la hinchazón persisten durante 7 días o si
desarrolla una infección o erupción cutánea, suspenda su uso y consultar al médico.

INGREDIENTS: Water, Menthol, Propylene Glycol, Triethanolamine, Carbomer, Aloe Barbadensis Leaf Extract.

Afassco¦ ¦® ANSI Z308.1 Manufactured for Afassco, Inc., Minden, NV 89423

6 70254 20388 7

6 Count Box Label

24 Count Box Label

Packet Label

res